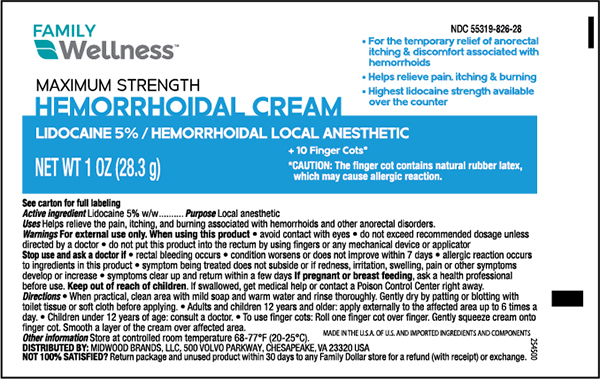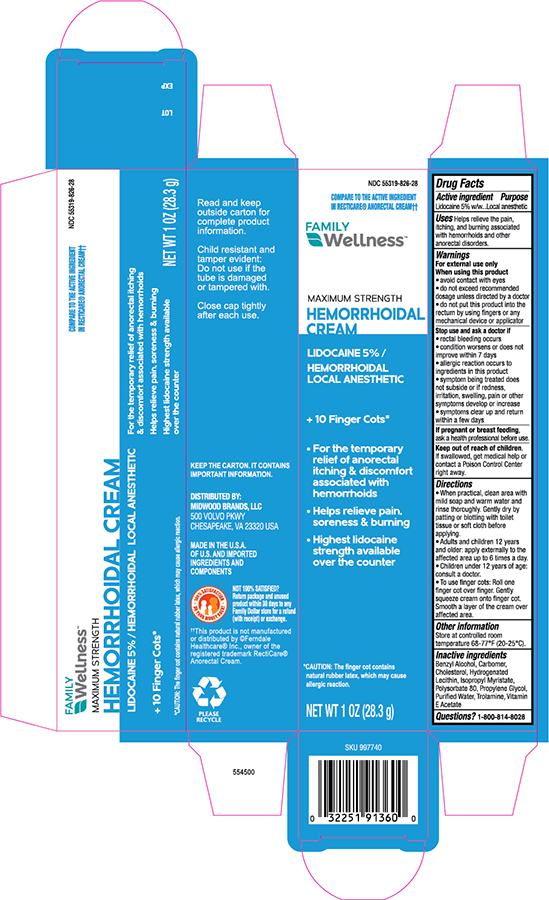 DRUG LABEL: Family Wellness Anorectal Lidocaine
NDC: 55319-826 | Form: CREAM
Manufacturer: FAMILY DOLLAR (Family Wellness)
Category: otc | Type: HUMAN OTC DRUG LABEL
Date: 20241121

ACTIVE INGREDIENTS: LIDOCAINE 50 mg/1 g
INACTIVE INGREDIENTS: PROPYLENE GLYCOL; HYDROGENATED SOYBEAN LECITHIN; TROLAMINE; ISOPROPYL MYRISTATE; BENZYL ALCOHOL; CARBOMER HOMOPOLYMER, UNSPECIFIED TYPE; POLYSORBATE 80; .ALPHA.-TOCOPHEROL ACETATE; CHOLESTEROL; WATER

Family Wellness Anorectal Lidocaine Cream

Active ingredient

Lidocaine 5 % w/w

Purpose

Local Anesthetic

Uses

Helps relieve the pain, itching, and burning associated with hemorrhoids and other anorectal disorders.

Warnings

For external use only.

When using this product

- avoid contact with eyes
- do not exceed recommended dosage unless directed by a doctor
- do not put this product into the rectum by using fingers or any mechanical device or applicator

Stop use and ask a doctor if

- rectal bleeding occurs
- condition worsens or does not improve within 7 days
- allergic reaction occurs to ingredients in this product
- symptom being treated does not subside or if redness, irritation, swelling, pain or other symptoms develop or increase
- symptoms clear up and return within a few days

Keep out of reach of children.
If swallowed, get medical help or contact a Poison Control Center right away.

Directions

- When practical, clean area with mild soap and warm water and rinse thoroughly. Gently dry by patting or blotting with toilet tissue or soft cloth before applying.
- Adults and children 12 years and older: apply externally to the affected area up to 6 times a day.
- Children under 12 years of age: consult a doctor.
- To use finger cots: Roll one finger cot over finger. Gently squeeze cream onto finger cot. Smooth a layer of the cream over affected area.

Other information

Store at controlled room temperature 68-77° F (20-25 °C)

Inactive ingredient

Benzyl Alcohol, Carbomer, Cholesterol, Hydrogenated Lecithin, Isopropyl Myristate, Polysorbate 80, Propylene Glycol, Purified Water, Trolamine, Vitamin E Acetate

Principal display panel -Tube

Family Wellness NDC 55319-826-28

HEMORRHOIDAL CREAM

Lidocaine 5%

NET WT 1 OZ (28.3g)

Principal Display Panel -Carton

Family Wellness NDC 55319-826-28

HEMORRHOIDAL CREAM

Lidocaine 5%

NET WT 1 OZ (28.3g)